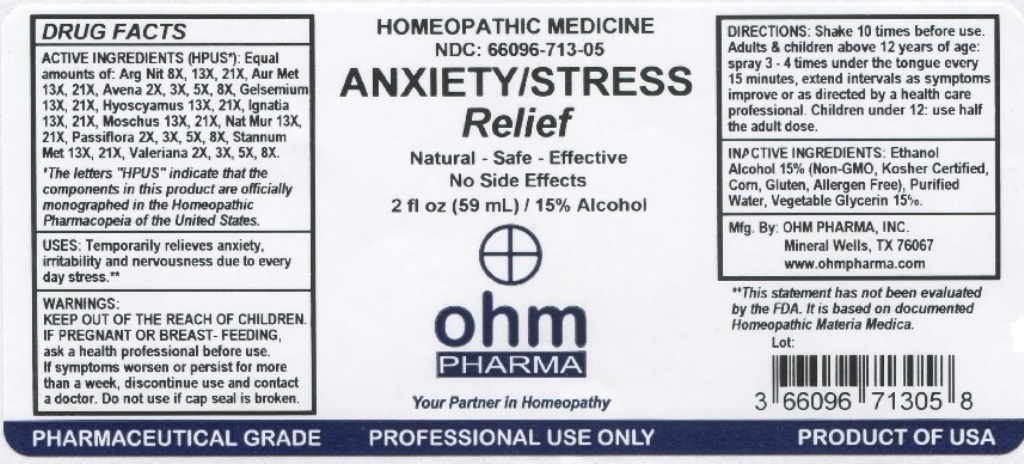 DRUG LABEL: Anxiety Stress Relief
NDC: 66096-713 | Form: LIQUID
Manufacturer: OHM PHARMA INC.
Category: homeopathic | Type: HUMAN OTC DRUG LABEL
Date: 20211229

ACTIVE INGREDIENTS: SILVER NITRATE 8 [hp_X]/59 mL; GOLD 13 [hp_X]/59 mL; AVENA SATIVA FLOWERING TOP 2 [hp_X]/59 mL; GELSEMIUM SEMPERVIRENS ROOT 13 [hp_X]/59 mL; HYOSCYAMUS NIGER 13 [hp_X]/59 mL; STRYCHNOS IGNATII SEED 13 [hp_X]/59 mL; MOSCHUS MOSCHIFERUS WHOLE 13 [hp_X]/59 mL; SODIUM CHLORIDE 13 [hp_X]/59 mL; PASSIFLORA INCARNATA TOP 2 [hp_X]/59 mL; TIN 13 [hp_X]/59 mL; VALERIAN 2 [hp_X]/59 mL
INACTIVE INGREDIENTS: ALCOHOL; WATER; GLYCERIN

OHM Anxiety/ Stress Relief

ACTIVE INGREDIENT

ACTIVE INGREDIENTS (HPUS*): Equal amounts of: Arg Nit 8X, 13X, 21X, Aur Met 13X, 21X, Avena 2X, 3X, 5X, 8X, Gelsemium 13X, 21X, Hyoscyamus 13X, 21X, Ignatia 13X, 21X, Moschus 13X, 21X, Nat Mur 13X, 21X, Passiflora 2X, 3X, 5X, 8X, Stannum Met 13X, 21X, Valeriana 2X, 3X, 5X, 8X.

*The letters "HPUS" indicate that the components in this product are officially monographed in the Homeopathic Pharmacopeia of the United States.

INDICATIONS AND USAGE

USES: Temporarily relieves anxiety, irritability and nervousness due to every day stress.**

**This statement has not been evaluated by the FDA. It is based on documented Homeopathic Materia Medica.

WARNINGS

WARNINGS: IF PREGNANT OR BREAST-FEEDING, ask a health professional before use. If symptoms worsen or persist for more than a week, discontinue use and contact a doctor.

- KEEP OUT OF REACH OF CHILDREN.

DOSAGE AND ADMINISTRATION

DIRECTIONS: Shake 10 times before use. Adults & children above 12 years of age: spray 3-4 times under the tongue every 15 minutes, extend intervals as symptoms improve or as directed by a health care professional. Children under 12: use half the adult dose.

Do not use if cap seal is broken.

INACTIVE INGREDIENT

INACTIVE INGREDIENTS: Ethanol Alcohol 15% (Non-GMO, Kosher Certified, Corn, Gluten, Allergen Free), Purified Water, Vegetable Glycerin 15%.

QUESTIONS

Mfg. By: OHM PHARMA, INC. Mineral Wells, TX 76067

www.ohmpharma.com

PACKAGE LABEL

HOMEOPATHIC MEDICINE

NDC: 66096-713-05

ANXIETY/STRESS Relief

Natural - Safe - Effective

No Side Effects

2 fl oz (59mL) / 15% Alcohol

PRODUCT OF USA

PURPOSE

Temporarily relieves anxiety, irritability and nervousness.